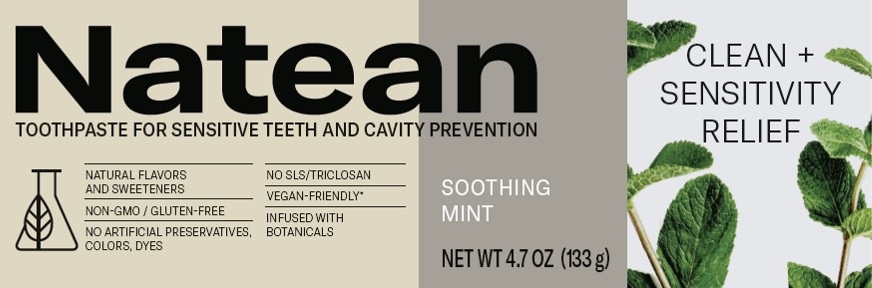 DRUG LABEL: NATEAN

NDC: 0135-1250 | Form: PASTE
Manufacturer: Haleon US Holdings LLC
Category: otc | Type: HUMAN OTC DRUG LABEL
Date: 20240319

ACTIVE INGREDIENTS: POTASSIUM NITRATE 50 mg/1 g; SODIUM FLUORIDE 1.5 mg/1 g
INACTIVE INGREDIENTS: WATER; HYDRATED SILICA; SORBITOL; GLYCERIN; COCAMIDOPROPYL BETAINE; SODIUM COCOYL GLUTAMATE; XANTHAN GUM; REBAUDIOSIDE A; COCONUT OIL; ALOE VERA LEAF; MALTODEXTRIN

Drug Facts

Active ingredients

Potassium nitrate 5%

Sodium fluoride 0.25% (0.15% w/v fluoride ion)

Purposes

Antihypersensitivity

Anticavity

Uses

- builds increasing protection against painful sensitivity of the teeth to cold, heat, acids, sweets, or contact.
- aids in the prevention of dental cavities.

Warnings

When using this product,if irritation occurs discontinue use.

Stop use and ask a dentist if

- the problem persists or worsens. Sensitive teeth may indicate a serious problem that may need prompt care by a dentist.
- pain/sensitivity still persists after 4 weeks of use.

Directions

- adults and children 12 years of age and older:
  - apply at least a 1-inch strip of the product onto a soft bristle toothbrush.
  - brush teeth thoroughly for at least 1 minute twice a day (morning and evening), and not more than 3 times a day, or as recommended by a dentist or doctor. Make sure to brush all sensitive areas of the teeth. Minimize swallowing. Spit out after brushing.
- Children under 12 years of age:Consult a dentist or doctor.

Other information

- do not store above 25°C (77F°)

Inactive ingredients

water, hydrated silica, sorbitol, glycerin, flavor, cocamidopropyl betaine, sodium cocoyl glutamate, xanthan gum, rebaudioside A, cocos nucifera (coconut) oil, aloe barbadensis leaf extract, maltodextrin

Questions or comments?

1-800-733-5879

Additional Information

ALWAYS FOLLOW THE LABEL

Natean was created by a small passionate team of scientists and herbalists on a mission to give you the best of what nature and science can offer, while minimizing our impact to the planet. Our toothpastes expertly balance powerful, scientifically studied ingredients with botanicals for a clean you can feel, and a clean you can feel good about.

NATEAN-INSPIRED BY NATURE AND DESIGNED TO BE CLEAN

RELIEVES SENSITIVE TEETH AND LEAVES YOUR MOUTH FEELING CLEAN AND FRESH

- Infused with natural orange blossom and mint flavor, and extracts from aloe vera and coconut
- Contains fluoride to fight cavities
- Helps control tartar build-up with twice daily brushing

*No animal origin materials used in the processing of these products. Contains no animal ingredients or derivatives.

†Recycling facilities for this product may not exist in your area

BPA-FREE TUBE

Tube contains post consumer recycled plastic

Recycleable carton, tube & cap

Distributed by: Alacer Corp.Carlisle, PA 17013

© 2021 Alacer Corp.

www.nateantoothpaste.com

Principal Display Panel

NDC 0135-1250-01

Natean

TOOTHPASTE FOR SENSITIVE TEETH AND CAVITY PREVENTION

NATURAL FLAVORS AND SWEETENERS

NON-GMO / GLUTEN-FREE

NO ARTIFICIAL PRESERVATIVES,

COLORS, DYES

NO SLS/TRICLOSAN

VEGAN-FRIENDLY*

INFUSED WITH

BOTANICALS

CLEAN + SENSITIVITY RELIEF

SOOTHING MINT

NET WT 4.7 OZ (133g)

1001587 Front Carton